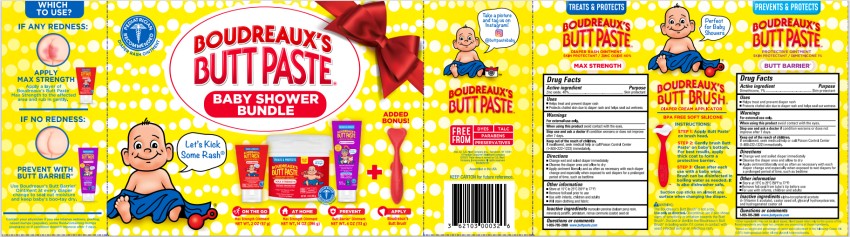 DRUG LABEL: Boudreauxs Baby Shower Bundle
NDC: 0132-0327 | Form: KIT | Route: TOPICAL
Manufacturer: C.B. Fleet Company, Inc.
Category: otc | Type: HUMAN OTC DRUG LABEL
Date: 20251027

ACTIVE INGREDIENTS: ZINC OXIDE 40 g/113 g; ZINC OXIDE 40 g/113 g; DIMETHICONE 1 g/113 g
INACTIVE INGREDIENTS: BALSAM PERU; CASTOR OIL; MINERAL OIL; PARAFFIN; PETROLATUM; BALSAM PERU; CASTOR OIL; MINERAL OIL; PARAFFIN; PETROLATUM; .ALPHA.-TOCOPHEROL ACETATE; GLYCERYL HYDROXYSTEARATE; HYDROGENATED CASTOR OIL; CASTOR OIL

Boudreauxs Butt Paste Baby Shower Bundle 0132-0327

MAX STRENGTH BOUDREAUX’S BUTT PASTE ®

DIAPER RASH OINTMENT

SKIN PROTECTANT (ZINC OXIDE)

Drug Facts

Purpose

Zinc oxide, 40%...................................................Skin protectant

Uses

- Helps treat and prevent diaper rash
- Protects chafed skin due to diaper rash and helps seal out wetness

Warnings

For external use only

Keep out of the reach of children.

If swallowed, seek medical help or call Poison Control Center (1-800-222-1222) immediately.

Directions

- Change wet and soiled diaper immediately
- Cleanse the diaper area and allow to dry
- Apply ointment liberally and as often as necessary with each diaper change and especially when exposed to wet diapers for a prolonged period of time, such as bedtime

Other information

- Store at 15°C to 25°C (59°F to 77°F)
- Remove foil seal prior to use
- Use with infants, children and adults
- Will stain clothing and fabric

Inactive ingredients

myroxylon pereiraie (balsam peru) resin, mineral oil, paraffin, petrolatum, ricinus communis (castor) seed oil

Questions or comments

1-855-785-2888 www.buttpaste.com

BOUDREAUX’S BUTT PASTE ® Butt Barrier

Protective Ointment

SKIN PROTECTANT (DIMETHICONE)

Drug Facts

Purpose

Dimethicone, 1% ...................................................Skin protectant

Uses

- Helps treat and prevent diaper rash
- Protects chafed skin due to diaper rash and helps seal out wetness

Warnings

For external use only.

Keep out of the reach of children.

If swallowed, seek medical help or call Poison Control Center (1-800-222-1222) immediately.

Directions

- Change wet and soiled diaper immediately
- Cleanse the diaper area and allow to dry
- Apply ointment liberally and as often as necessary with each diaper change and especially when exposed to wet diapers for a prolonged period of time, such as bedtime

Other information

- Store at 15°C to 25°C (59°F to 77°F)
- Remove foil seal from tube’s tip before use
- For use with infants, children and adults

Inactive ingredients

Alpha-tocopherol actate d- (Vitamin E acetate), castor seed oil, glyceryl hydroxystearate, and hydrogenated castor oil

Questions or comments

1-855-785-2888 www.buttpaste.com

BOUDREAUX’S® BUTT BRUSH

DIAPER CREAM APPLICATOR

BPA FREE SILICONE

Instructions:

Step 1: Apply Butt Paste® on brush head.

Step 2: Gently brush Butt Paste® on baby’s bottom. For best results, apply thick coat to form a protective barrier.

Step 3: Clean after each use with a baby wipe. Brush can be disinfected in boiling water as needed. It is also dishwasher safe.

Suction cup sticks on almost any surface when changing the diaper.

WARNING:

The Boudreaux’s Butt Brush™ is not a toy. Use only as directed. Discontinue use if skin shows signs of sensitivity or irritation towards the Boudreaux’s Butt Brush™. Discard or sterilize the Boudreaux’s Butt Brush™ in boiling water if comes in contact with yeast infected skin or an infectious rash.

Principal display panel

BOUDREAUX’S® Baby Shower Bundle

KIT INCLUDES:

-Maximum Strength Boudreaux’s Butt Paste® -NET WT. 2oz (57 g)

-Maximum Strength Boudreaux’s Butt Paste®- NET WT. 14oz (396 g)

-Boudreaux’s Butt Paste Butt Barrier -NET WT. 4 oz (113 g)

-Boudreaux’s Butt Brush™